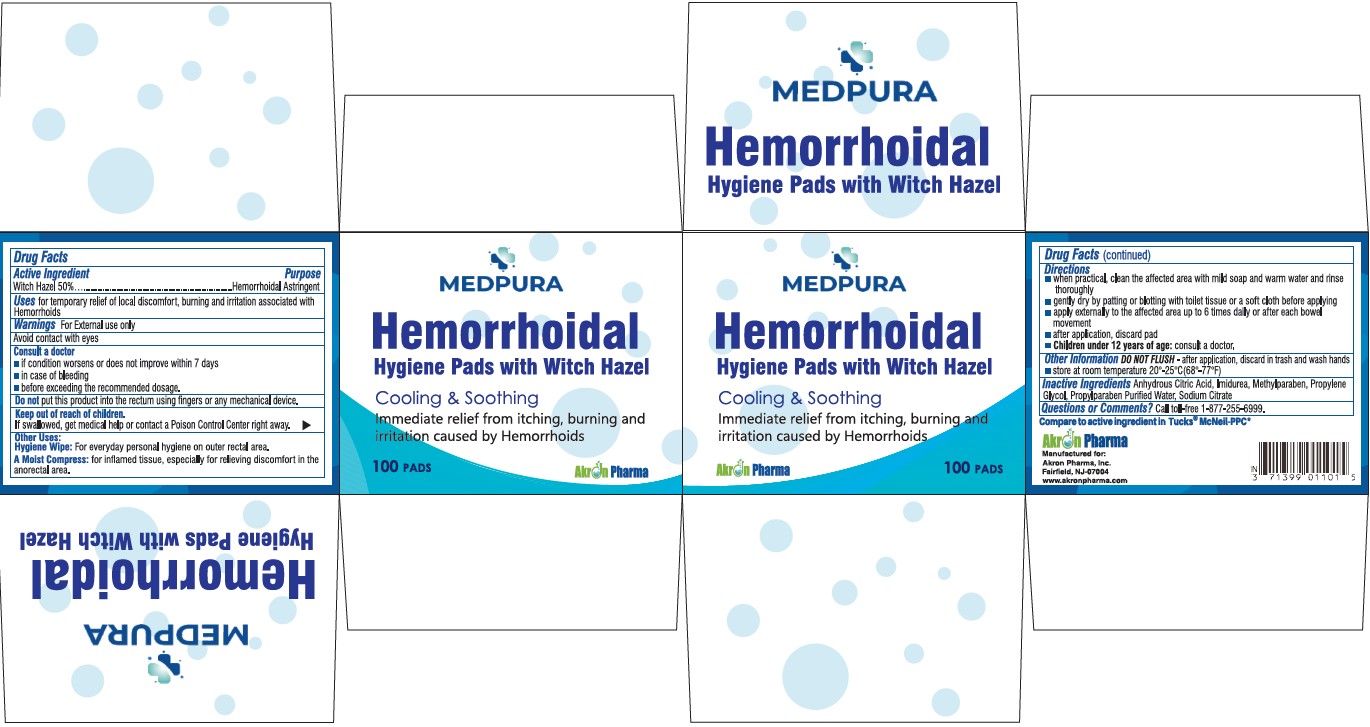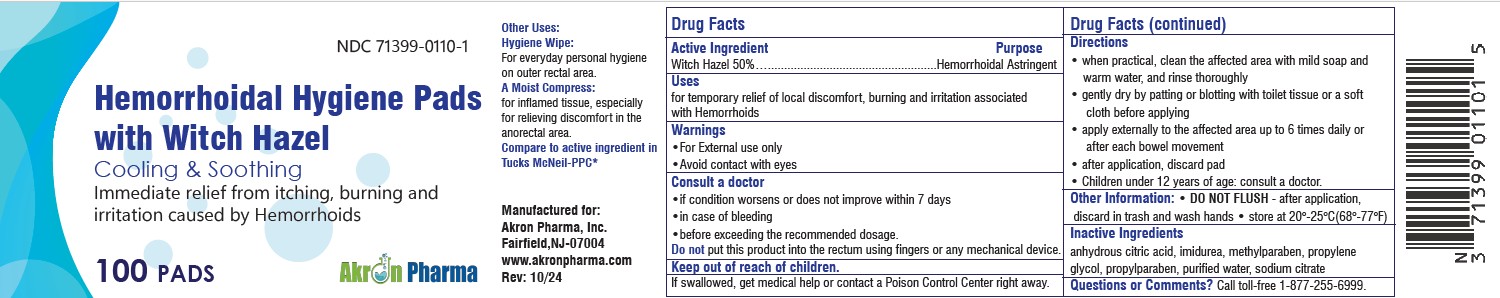 DRUG LABEL: Hemorrhoidal Hygiene pads
NDC: 71399-0110 | Form: SOLUTION
Manufacturer: Akron Pharma Inc.
Category: otc | Type: HUMAN OTC DRUG LABEL
Date: 20260112

ACTIVE INGREDIENTS: WITCH HAZEL 50 g/100 mL
INACTIVE INGREDIENTS: IMIDUREA; METHYLPARABEN; PROPYLPARABEN; SODIUM CITRATE; WATER; ANHYDROUS CITRIC ACID; PROPYLENE GLYCOL

Cooling & Soothing
Immediate relief from itching, burning and irritation
caused by Hemorrhoids.
100 PADS

Drug Facts

Witch Hazel 50%
Purpose: Hemorrhoidal Astringent

Uses

For temporary relief of local discomfort,
burning and irritation associated with Hemorrhoids

WARNINGS

For External Use Only

- Avoid contact with the eyes

Consult a doctor

- If condition worsens or does not improve within 7 days
- In case of bleeding
- Before exceeding the recommended dosage

DO NOTput this product into the rectum using fingers or any mechanical device.

KEEP OUT OF REACH OF CHILDREN

- If swallowed, get medical attention or contact the Poison Control Center immediately.

Directions:

- When practical, clean the affected area with mild soap and warm water, and rinse thoroughly

DOSAGE AND ADMINISTRATION

- Gently dry by patting or blotting with toilet tissue or a soft cloth before applying
- Apply externally to the affected area up to 6 times daily or after each bowel movement
- After application, discard pad Children under 12 years of age: consult a doctor

Other Information

- Store at room temperature 15°-30°C (59°-86°F)
- If adverse effects call 1-877-225-6999

Other Ingredients

Alcohol, Citric Acid, Deionized Water, DMDM Hydantoin,Glycerin, Sodium Citrate.